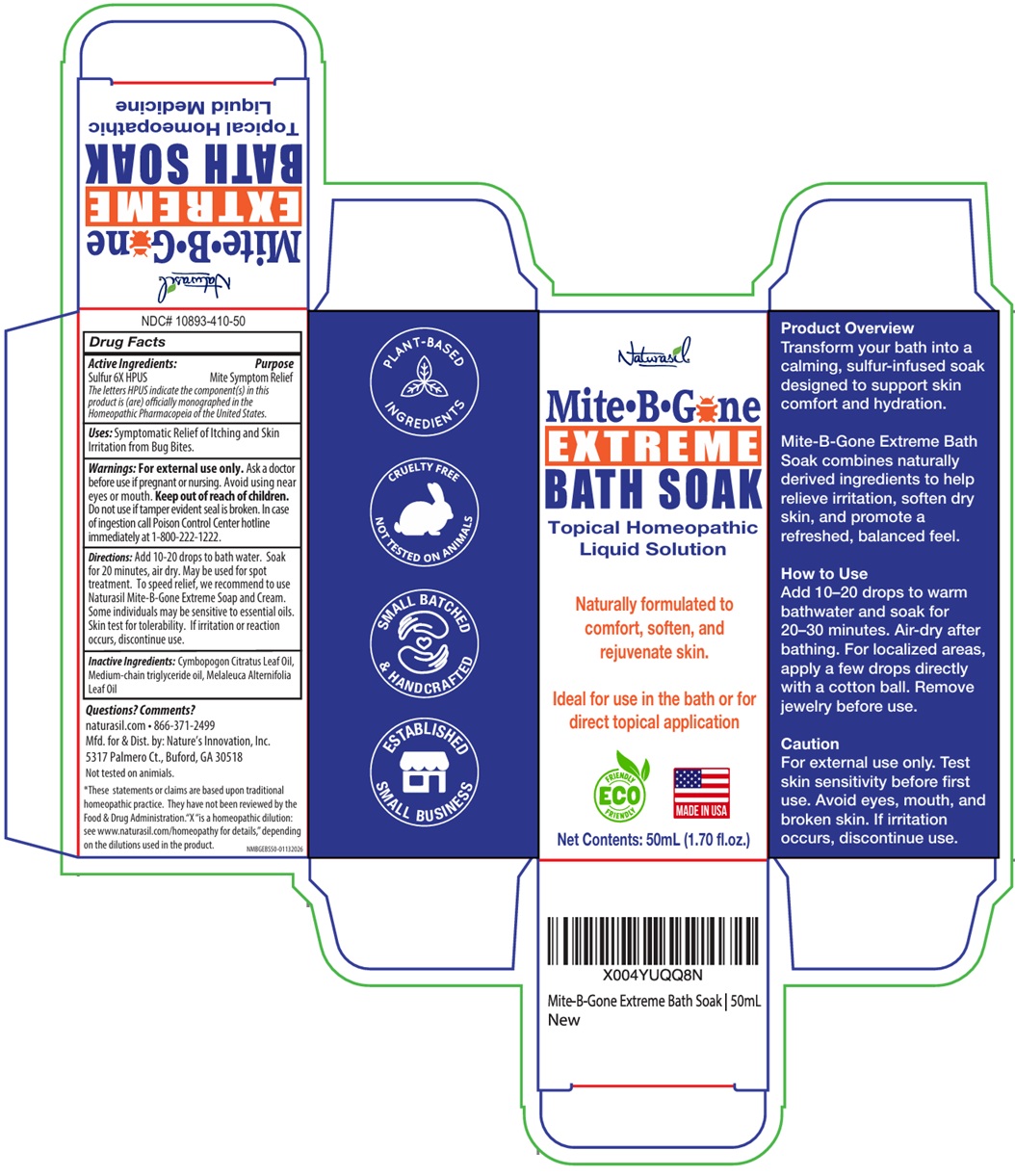 DRUG LABEL: Naturasil Mite B Gone EXTREME BATH SOAK
NDC: 10893-410 | Form: LIQUID
Manufacturer: Nature's Innovation, Inc.
Category: homeopathic | Type: HUMAN OTC DRUG LABEL
Date: 20260120

ACTIVE INGREDIENTS: SULFUR 6 [hp_X]/1 mL
INACTIVE INGREDIENTS: WEST INDIAN LEMONGRASS OIL; MEDIUM-CHAIN TRIGLYCERIDES; TEA TREE OIL

Naturasil Mite•B•Gone EXTREME BATH SOAK

Active Ingredients:

Sulfur 6X HPUS

The letters HPUS indicate the component(s) in this product is (are) officially monographed in the Homeopathic Pharmacopeia of the United States.

Purpose

Mite Symptom Relief

Uses:

Symptomatic Relief of Itching and Skin Irritation from Bug Bites.

Warnings:

For external use only. Ask a doctor before use if pregnant or nursing. Avoid using near eyes or mouth.

Keep out of reach of children. Do not use if tamper evident seal is broken. In case of ingestion call Poison Control Center hotline immediately at 1-800-222-1222.

Directions:

Add 10-20 drops to bath water. Soak for 20 minutes, air dry. May be used for spot treatment. To speed relief, we recommend to use Naturasil Mite-B-Gone Extreme Soap and Cream. Some individuals may be sensitive to essential oils. Skin test for tolerability. If irritation or reaction occurs, discontinue use.

Inactive Ingredients:

Cymbopogon Citratus Leaf Oil, Medium-chain triglyceride oil, Melaleuca Alternifolia Leaf Oil

Questions? Comments?

naturasil.com • 866-371-2499

Topical Homeopathic Liquid Solution

Naturally formulated to comfort, soften, and rejuvenate skin.

Ideal for use in the bath or for direct topical application

ECO FRIENDLY

MADE IN USA

Product Overview
Transform your bath into a calming, sulfur-infused soak designed to support skin comfort and hydration.

Mite-B-Gone Extreme Bath Soak combines naturally derived ingredients to help relieve irritation, soften dry skin, and promote a refreshed, balanced feel.

How to use
Add 10-20 drops to warm bathwater and soak for 20-30 minutes. Air-dry after bathing. For localized areas, apply a few drops directly with a cotton ball. Remove jewelry before use.

Caution
For external use only. Test skin sensitivity before first use. Avoid eyes, mouth, and broken skin. If irritation occurs, discontinue use.

Mfd. for & Dist. by: Nature's Innovation, Inc.
5317 Palmero Ct., Buford, GA 30518

Not tested on animals.

*These statements or claims are based upon traditional homeopathic practice. They have not been reviewed by the Food & Drug Administration. "X" is a homeopathic dilution: see www.naturasil.com/homeopathy for details," depending on the dilutions used in the product.

PLANT-BASED INGREDIENTS

CRUELTY FREE
NOT TESTED IN ANIMALS

SMALL BATCHED & HANDCRAFTED

ESTABLISHED SMALL BUSINESS